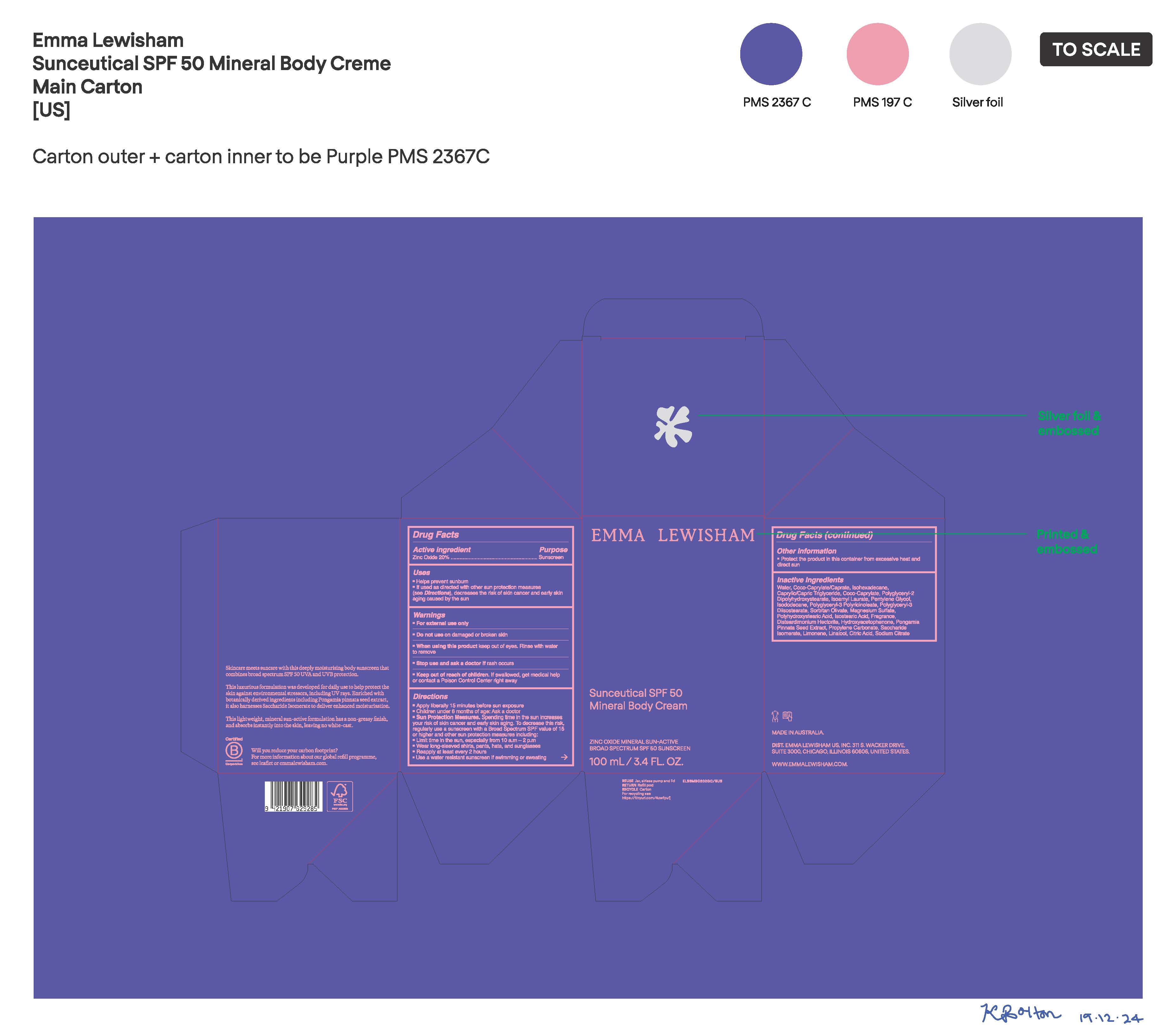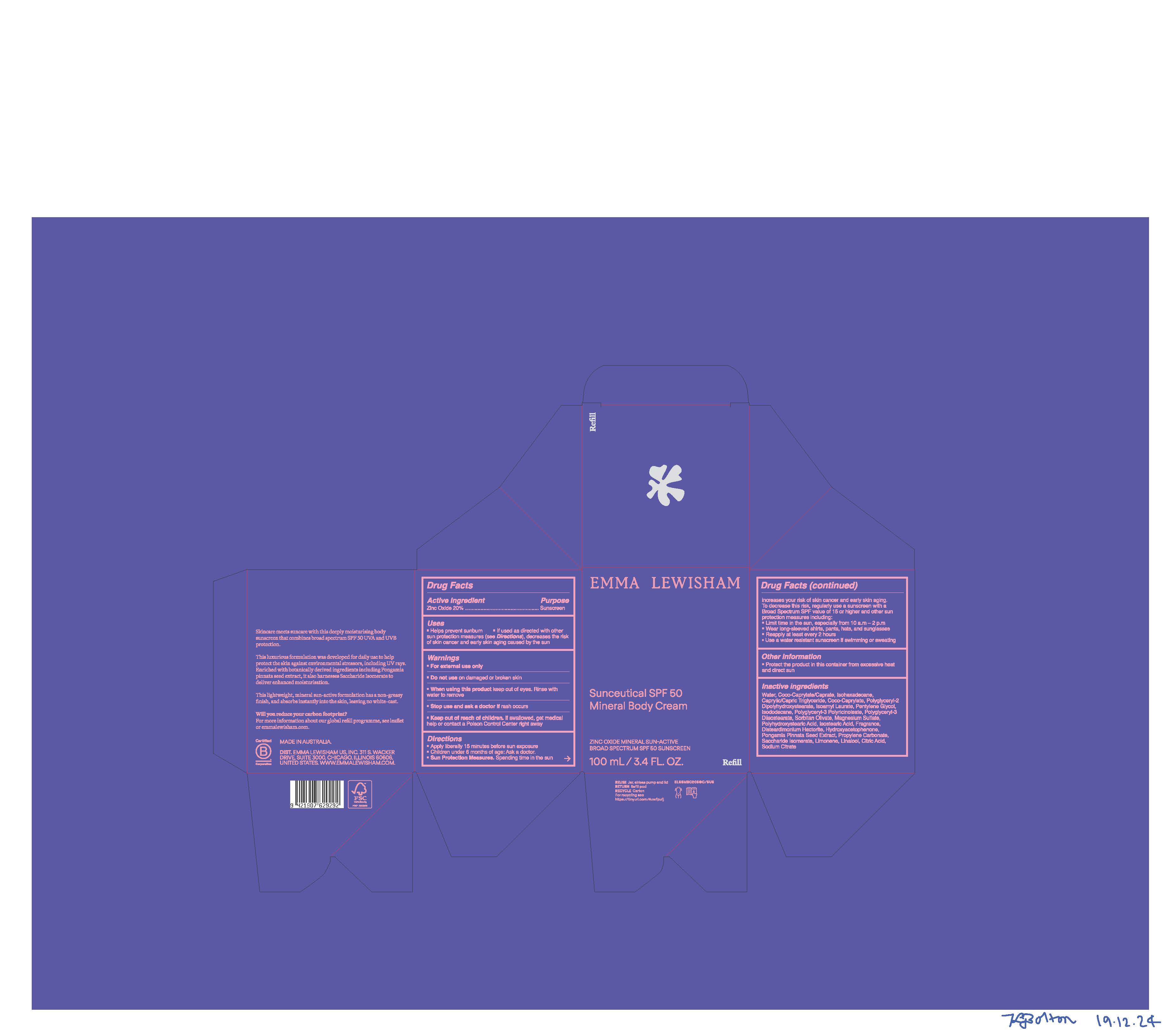 DRUG LABEL: Sunceutical SPF 50 Mineral Body Cream
NDC: 70157-368 | Form: CREAM
Manufacturer: Baxter Laboratories Pty. Ltd.
Category: otc | Type: HUMAN OTC DRUG LABEL
Date: 20250120

ACTIVE INGREDIENTS: ZINC OXIDE 20 g/100 mL
INACTIVE INGREDIENTS: POLYGLYCERYL-3 DIISOSTEARATE; SORBITAN OLIVATE; POLYHYDROXYSTEARIC ACID (2300 MW); LIMONENE, (+)-; COCO-CAPRYLATE/CAPRATE; PONGAMIA PINNATA SEED; COCO-CAPRYLATE; PENTYLENE GLYCOL; HYDROXYACETOPHENONE; ISOHEXADECANE; MAGNESIUM SULFATE; ISOSTEARIC ACID; SODIUM CITRATE; POLYGLYCERYL-2 DIPOLYHYDROXYSTEARATE; POLYGLYCERYL-3 PENTARICINOLEATE; LINALOOL; CITRIC ACID; WATER; CAPRYLIC/CAPRIC TRIGLYCERIDE; SACCHARIDE ISOMERATE; ISOAMYL LAURATE; ISODODECANE; DISTEARDIMONIUM HECTORITE; PROPYLENE CARBONATE

Sunceutical SPF 50 Mineral Body Cream

Active Ingredient Purpose

Zinc Oxide 20% Sunscreen

Uses

- Helps prevent sunburn
- If used as directed with other sun protection measures (see Directions), decreases the risk of skin cancer and early skin aging caused by the sun

- Keep out of reach of children. If swallowfield, get medical help or contact a Poison Control Center right away.

Stop use and ask a doctor if rash occurs.

Warnings

- For external use only
- Do not use on damaged or broken skin
- When using this product keep out of eyes. Rinse with water to remove.

Directions

- Apply liberally 15 minutes before sun exposure
- Children under 6 months of age: Ask a doctor
- Sun Protection Measures. Spending time in the sun increases your risk of skin cancer and early skin aging. To decrease this risk, regularly use a sunscreen with a Broad Spectrum SPF value of 15 or higher and other sun protection measures including:
- Limit time in the sun, especially from 10 a.m. - 2 p.m.
- Wear long-sleeved shirts, pants, hats, and sunglasses
- Reapply at least every 2 hours
- Use a water resistant sunscreen if swimming or sweating

Other information

- Protect the product in this container from excessive heat and direct sun

Inactive ingredients

Water, Coco-Caprylate/Caprate, Isohexadecane, Caprylic/Capric Triglyceride, Coco-Caprylate, Polyglyceryl-2 Dipolyhydroxstearate, Isoamyl Laurate, Pentylene Glycol, Isododecane, Polyglyceryl- 3 Polyricinoleate, Polyglyceryl-3 Diisostearate, Sorbitan Olivate, Magnesium Sulfate, Polyhydroxystearic Acid, Isostearic Acid, Fragrance, Disteardimonium Hectorite, Hydroxyacetophenone, Pongamia Pinnata Seed Extract, Propylene Carbonate, Saccharide Isomerate, Limonene, Linalool, Citric Acid, Sodium Citrate

PACKAGE LABEL

Emma Lewisham

Sunceutical SPF 50

Mineral Body Cream

Zinc Oxide Mineral Sun-Active

Broad Spectrum SPF 50 Sunscreen

100 mL/ 3.4 FL. OZ.